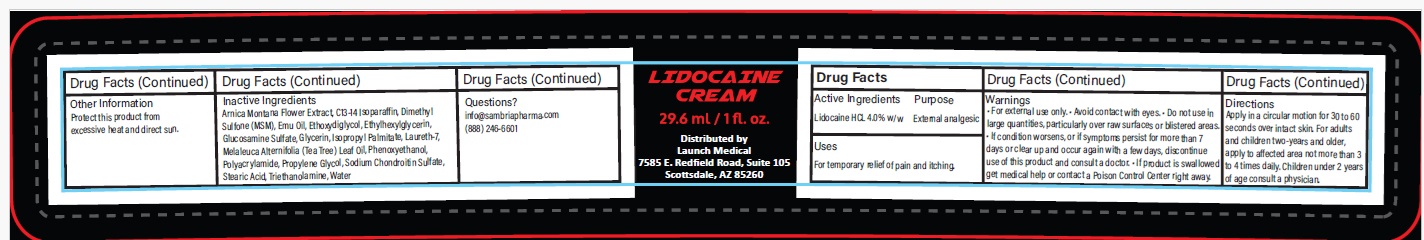 DRUG LABEL: Launch Medical
NDC: 54723-018 | Form: CREAM
Manufacturer: Sambria Pharmaceuticals, LLC
Category: otc | Type: HUMAN OTC DRUG LABEL
Date: 20251112

ACTIVE INGREDIENTS: LIDOCAINE HYDROCHLORIDE 4 g/100 mL
INACTIVE INGREDIENTS: ARNICA MONTANA FLOWER; C13-14 ISOPARAFFIN; DIMETHYL SULFONE; EMU OIL; DIETHYLENE GLYCOL MONOETHYL ETHER; ETHYLHEXYLGLYCERIN; GLUCOSAMINE SULFATE; GLYCERIN; ISOPROPYL PALMITATE; LAURETH-7; TEA TREE OIL; PHENOXYETHANOL; POLYACRYLAMIDE (10000 MW); PROPYLENE GLYCOL; SODIUM CHONDROITIN SULFATE (PORCINE; 5500 MW); STEARIC ACID; TROLAMINE; WATER

Active ingredient

Lidocaine HCL 4.0% w/w

Purpose

External Analgesic

Uses

For temporary relief of pain and itching.

Warnings

- For external use only.
- Avoid contact with eyes.
- Do not use in large quantities, particularly over raw surfaces or blistered areas.
- If condition worsens, or if symptoms persist for more than 7 days or clear up and occur again with a few days, discontinue use of this product and consult a doctor.
- If product is swallowed get medical help or contact a Poison Control Center right away.

Directions

- Apply in a circular motion for 30 to 60 seconds over intact skin.
- For adults and children two-years and older, apply to affected area not more than 3 to 4 times daily.
- Children under 2 years of age consult a physician.

Inactive ingredients

Arnica Montana Flower Extract, C13-14 Isoparaffin, Dimethyl Sulfone (MSM), Emu Oil, Ethoxydiglycol, Ethylhexylglycerin, Glucosamine Sulfate, Glycerin, Isopropyl Palmitate, Laureth-7, Melaleuca Alternifolia (Tea Tree) Leaf Oil, Phenoxyethanol, Polyacrylamide, Propylene Glycol, Sodium Chondroitin Sulfate, Stearic Acid, Triethanolamine, Water

Other information

Protect this product from excessive heat and direct sun.

Questions?

info@sambriapharma.com

(888) 246-6601